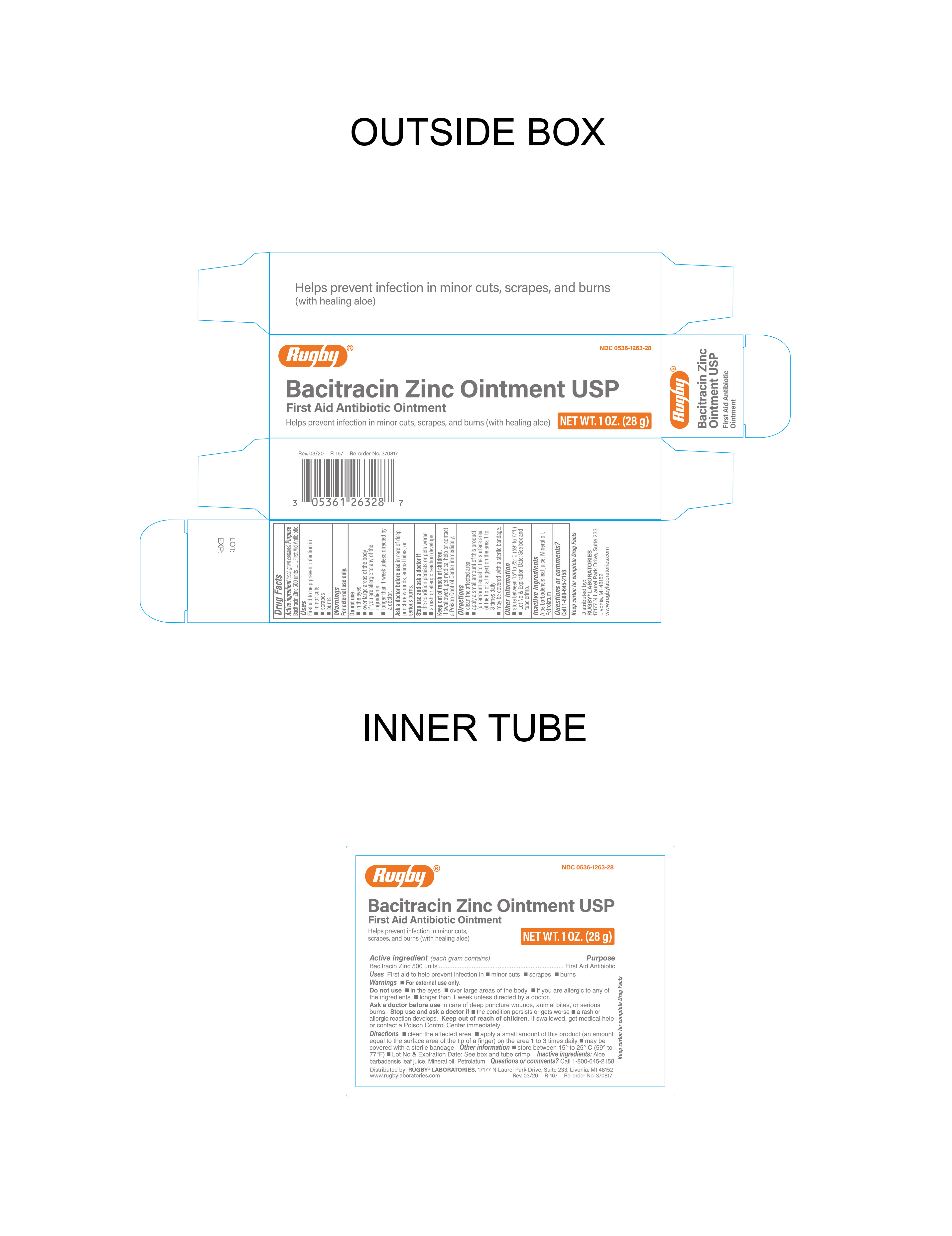 DRUG LABEL: Bacitracin Zinc
NDC: 0536-1263 | Form: OINTMENT
Manufacturer: Rugby Laboratories
Category: otc | Type: HUMAN OTC DRUG LABEL
Date: 20241217

ACTIVE INGREDIENTS: BACITRACIN ZINC 500 [USP'U]/1 g
INACTIVE INGREDIENTS: MINERAL OIL; PETROLATUM; ALOE VERA LEAF

Rugby Bacitracin Zinc Ointment

Active Ingredient

Bacitracin Zinc 500 Units per gram

Purpose

First Aid Antibiotic

Uses

First Aid to help prevent infection in

- minor cuts
- scrapes
- burns

Warnings

For External Use Only.

Do Not Use

- in eyes
- over large areas of the body
- if you are allergic to any of the ingredients
- longer than 1 week unless directed by a doctor

Ask Doctor before Use

In care of deep puncture wounds, animal bites, or serious burns.

Stop Use and Ask Doctor if

- The condition persists or gets worse
- A rash or allergic reaction develops

Directions

- Clean the affected area
- Apply a small amount of this product (an amount equal to the surface area of the tip of a finger) on the area 1 to 3 times daily
- May be covered with a sterile bandage

Inactive Ingredients

Aloe barbadensis leaf juice, mineral oil, petrolatum

Questions

Call 1-800-645-2158

Keep out of reach of children

If swallowed, get medical help or contact a Poison Control Center immediately.

Other Information

Store Between 15° to 25°C (59° to 77°F)

Lot No. and Expiration Date: See box and tube crimp

Distributed By:

RUGBY LABORATORIES

17177 N Laurel Park Drive, Suite 233

Livonia, MI 48152

www.rugbylaboratories.com

1-800-645-2158

Made in China